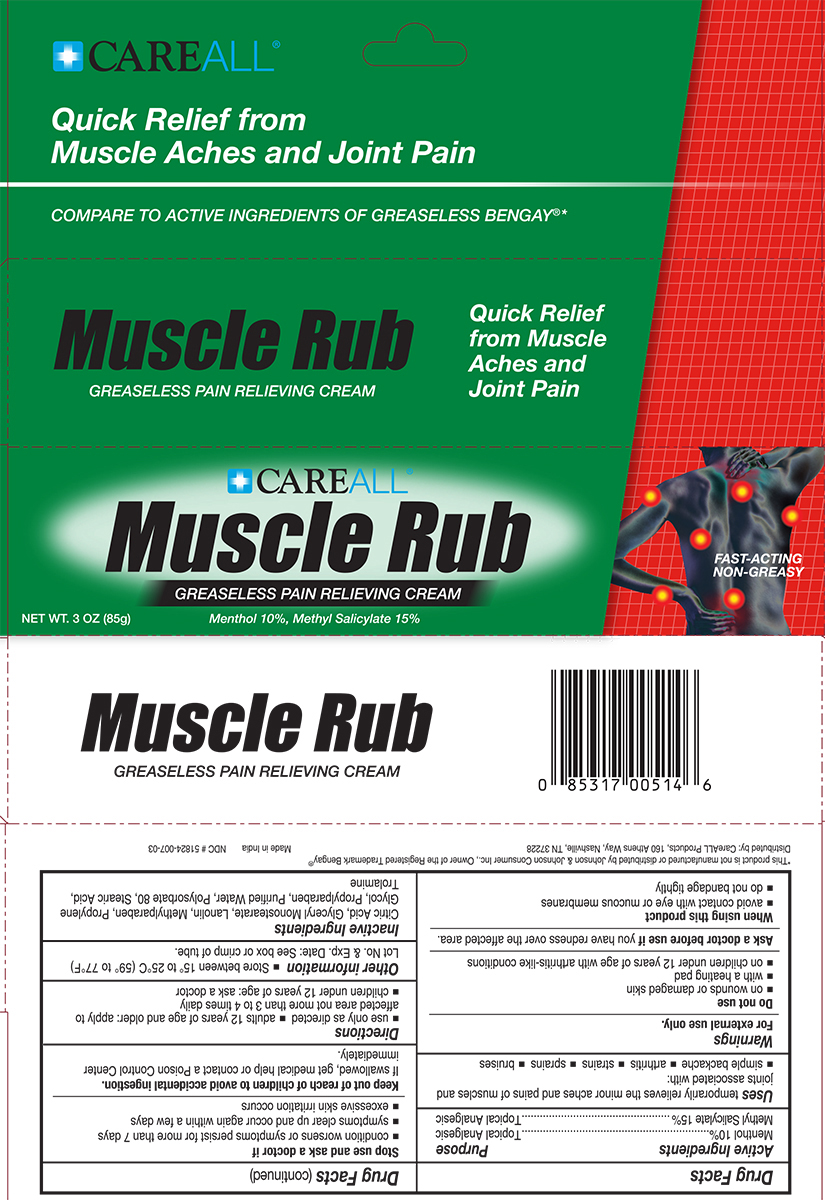 DRUG LABEL: CAREALL Muscle Rub

NDC: 51824-007 | Form: CREAM
Manufacturer: New World Imports, Inc
Category: otc | Type: HUMAN OTC DRUG LABEL
Date: 20251201

ACTIVE INGREDIENTS: MENTHOL 100 mg/1 g; METHYL SALICYLATE 150 mg/1 g
INACTIVE INGREDIENTS: CITRIC ACID MONOHYDRATE; GLYCERYL MONOSTEARATE; METHYLPARABEN; PROPYLENE GLYCOL; PROPYLPARABEN; WATER; STEARIC ACID; TROLAMINE; LANOLIN; POLYSORBATE 80

Drug Facts

ACTIVE INGREDIENT

Menthol

Methyl Salicylate

PURPOSE

Topical analgesic

Keep out of reach of children to avoid accidental ingestion.If swallowed, get medical help or contact a Poison Control Center Immediately.

INDICATIONS AND USAGE

Temporarily relieves the minor aches and pains of muscles and joints associated with simple backache, arthritis, strains, bruises, and sprains.

WARNINGS

For external use only

Do not use:

On wounds or damaged skin

With a heating pad

On a child under 12 years of age with arthritis-like conditions

Ask a doctor before use if you have

redness over the affected area

When using this product

Avoid contact with eyes or mucous membrane

Do not bandage tightly

Stop use and ask a doctor if

Condition worsens or symptoms persist for more than 7 days

Symptoms clear up and occur again within a few days

Excessive skin irritation occurs

DOSAGE AND ADMINISTRATION

Use only as directed

Adults and children 12 years of age and older; apply to affected area not more than 3 to 4 times daily

Children under 12 years of age: ask a doctor

INACTIVE INGREDIENT

Citric Acid, Glyceryl Monostearate, Lanolin, Methylparaben, Propylene Glycol, Propylparaben, Purified Water, Polysorbate 80, Stearic Acid, Trolamine